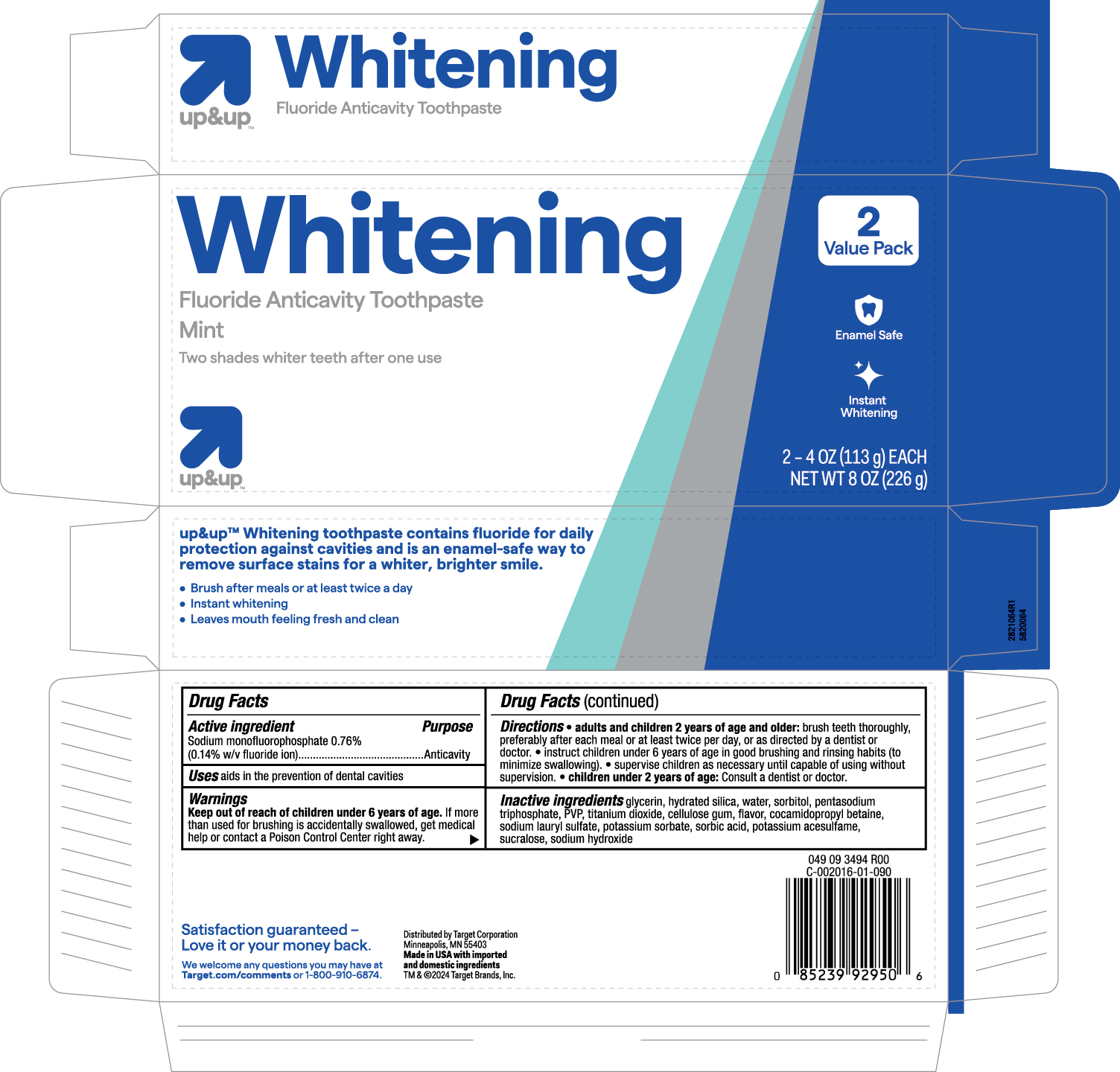 DRUG LABEL: Whitening
NDC: 11673-385 | Form: PASTE, DENTIFRICE
Manufacturer: Target
Category: otc | Type: HUMAN OTC DRUG LABEL
Date: 20251121

ACTIVE INGREDIENTS: SODIUM MONOFLUOROPHOSPHATE 0.14 g/100 g
INACTIVE INGREDIENTS: SORBITOL; SODIUM HYDROXIDE; POTASSIUM SORBATE; HYDRATED SILICA; SUCRALOSE; SORBIC ACID; WATER; GLYCERIN; TITANIUM DIOXIDE; SODIUM LAURYL SULFATE; COCAMIDOPROPYL BETAINE

5820082 Target Whitening Toothpaste (8070491)

Active ingredient

Sodium monofluorophosphate 0.76% w/w (0.14% w/v fluoride ion)

Purpose

Anticavity

Uses

aids in the prevention of dental cavities

Keep out of reach of children under 6 years of age. If more than used for brushing is accidentally swallowed, get medical help or contact a Poison Control Center right away.

Directions

adults and children 2 years of age and older: brush teeth thoroughly, preferably after ach meal or at least twice per day, or as directed by a dentist or doctor.

instruct children under 6 years of age in good brushing and rinsing habits (to minimize swallowing).

supervise children as necessary until capable of using without supervision.

children under 2 years of age: Consult a dentist or doctor.

Inactive ingredients

glycerin, hydrated silica, water, sorbitol, pentasodium triphosphate, PVP, titanium dioxide, cellulose gum, flavor, cocamidopropyl betaine, sodium lauryl sulfate, potassium sorbate, sorbic acid, potassium acesulfam, sucralose, sodium hydroxide

Warnings

Keep out of reach of children under 6 years of age. If more than used for brushing is accidentally swallowed, get medical help or contact a Poison Control Center right away.